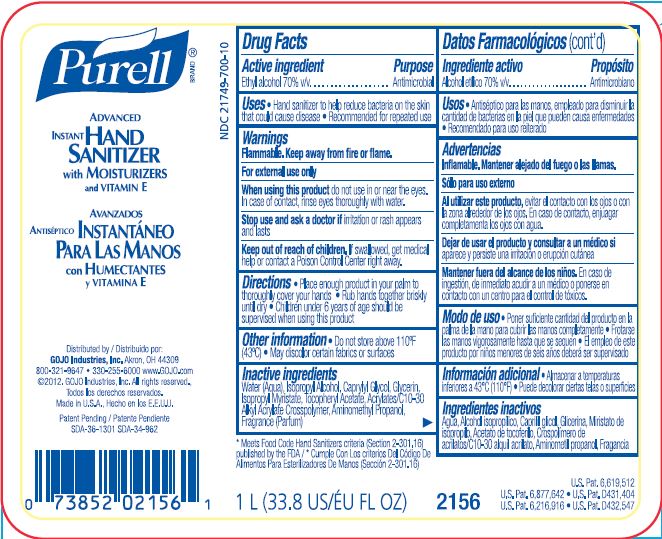 DRUG LABEL: PURELL Advanced Instant Hand Sanitizer
NDC: 21749-700 | Form: LIQUID
Manufacturer: GOJO Industries, Inc.
Category: otc | Type: HUMAN OTC DRUG LABEL
Date: 20260112

ACTIVE INGREDIENTS: ALCOHOL 0.7 mL/1 mL
INACTIVE INGREDIENTS: WATER; ISOPROPYL ALCOHOL; GLYCERIN; ISOPROPYL MYRISTATE; .ALPHA.-TOCOPHEROL ACETATE, D-; CAPRYLYL GLYCOL; AMINOMETHYLPROPANOL

PURELL Advanced Hand Sanitizer

Active ingredient

Ethyl alcohol 70%

Purpose

Antimicrobial

Use

Hand sanitizer to help reduce bacteria on the skin that could cause disease

Warnings

Flammable. Keep away from fire or flame.

For external use only

WHEN USING

When using this productdo not use in or near the eyes. In case of contact, rinse eyes thoroughly with water.

Stop use and ask a doctor ifirritation or rash appears and lasts

Keep out of reach of children.If swallowed, get medical help or contact a Poison Control Center right away.

Directions

Place enough product in your palm to thoroughly cover your hands

Rub hands together briskly until dry

Children under 6 years of age should be supervised when using this product

Inactive ingredients

Water (Aqua), Isopropyl Alcohol, Caprylyl Glycol, Glycerin, Isopropyl Myristate, Tocopheryl Acetate, Acrylates/C10-30 Alkyl Acrylate Crosspolymer, Aminomethyl Propanol, Fragrance (Parfum)